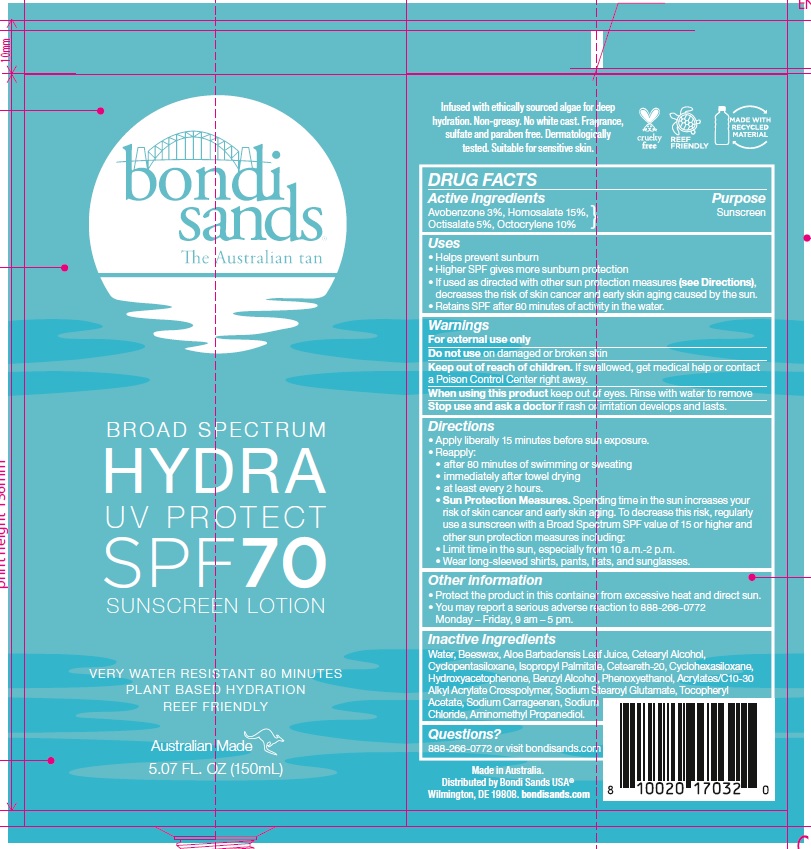 DRUG LABEL: Bondi Sands Broad Spectrum Hydra UV Protect SPF 70 Sunscreen
NDC: 70157-018 | Form: LOTION
Manufacturer: Baxter Laboratories Pty. Ltd.
Category: otc | Type: HUMAN OTC DRUG LABEL
Date: 20240126

ACTIVE INGREDIENTS: AVOBENZONE 30 mg/1 mL; OCTOCRYLENE 100 mg/1 mL; HOMOSALATE 150 mg/1 mL; OCTISALATE 50 mg/1 mL
INACTIVE INGREDIENTS: CYCLOMETHICONE 6; POLYOXYL 20 CETOSTEARYL ETHER; HYDROXYACETOPHENONE; ISOPROPYL PALMITATE; SODIUM STEAROYL GLUTAMATE; PHENOXYETHANOL; AMINOMETHYL PROPANEDIOL; WATER; ALOE VERA LEAF; .ALPHA.-TOCOPHEROL ACETATE; CETOSTEARYL ALCOHOL; CARRAGEENAN; YELLOW WAX; SODIUM CHLORIDE; BENZYL ALCOHOL; CYCLOMETHICONE 5

Bondi Sands Broad Spectrum Hydra UV Protect SPF 70 Sunscreen Lotion

Active Ingredients

Avobenzone 3%, Homosalate 15%, Octisalate 5%, Octocrylene 10%

Purpose

Sunscreen

Uses

- Helps prevent sunburn
- Higher SPF gives more sunburn protection
- If used as directed with other sun protection measures (see Directions), decreases the risk of skin cancer and early skin aging caused by the sun.
- Retains SPF after 80 minutes of activity in the water.

Warnings

For external use only

Do not use on damaged or broken skin.

Stop use and ask a doctor if rash or irritation develops and lasts.

Keep out of reach of children.

If swallowed, get medical help or contact a Poison Control Center right away.

When using this product

keep out of eyes. Rinse with water to remove.

Directions

- Apply liberally 15 minutes before sun exposure.
- Reapply:
- after 80 minutes of swimming or sweating
- immediately after towel drying
- at least every 2 hours
- Sun Protection Measures. Spending time in the sun increases your risk of skin cancer and early skin aging. To decrease this risk, regularly use a sunscreen with a Broad Spectrum SPF value of 15 or higher and other sun protection measures including:
- Limit time in the sun, especially from 10 a.m.- 2 p.m.
- Wear long-sleeved shirts, pants, hats, and sunglasses.

Other information

- Protect the product in this container from excessive heat and direct sun.
- You may report a serious adverse reaction to 888-266-0772; Monday – Friday, 9 am – 5 pm.

Inactive Ingredients

Water, Beeswax, Aloe Barbadensis Leaf Juice, Cetearyl Alcohol, Cyclopentasiloxane, Isopropyl Palmitate, Ceteareth-20, Cyclohexasiloxane, Hydroxyacetophenone, Benzyl Alcohol, Phenoxyethanol, Acrylates/C10-30 Alkyl Acrylate Crosspolymer, Sodium Stearoyl Glutamate, Tocopheryl Acetate, Sodium Carrageenan, Sodium Chloride, Aminomethyl Propanediol.

Questions?

888-266-0772 or visit bondisands.com

Product Packaging

bondi sands

The Australian tan

BROAD SPECTRUM

HYDRA

UV PROTECT

SPF 70

SUNSCREEN LOTION

VERY WATER RESISTANT 80 MINUTES

PLANT BASED HYDRATION

REEF FRIENDLY

Australian Made

5.07 FL. OZ. (150mL)